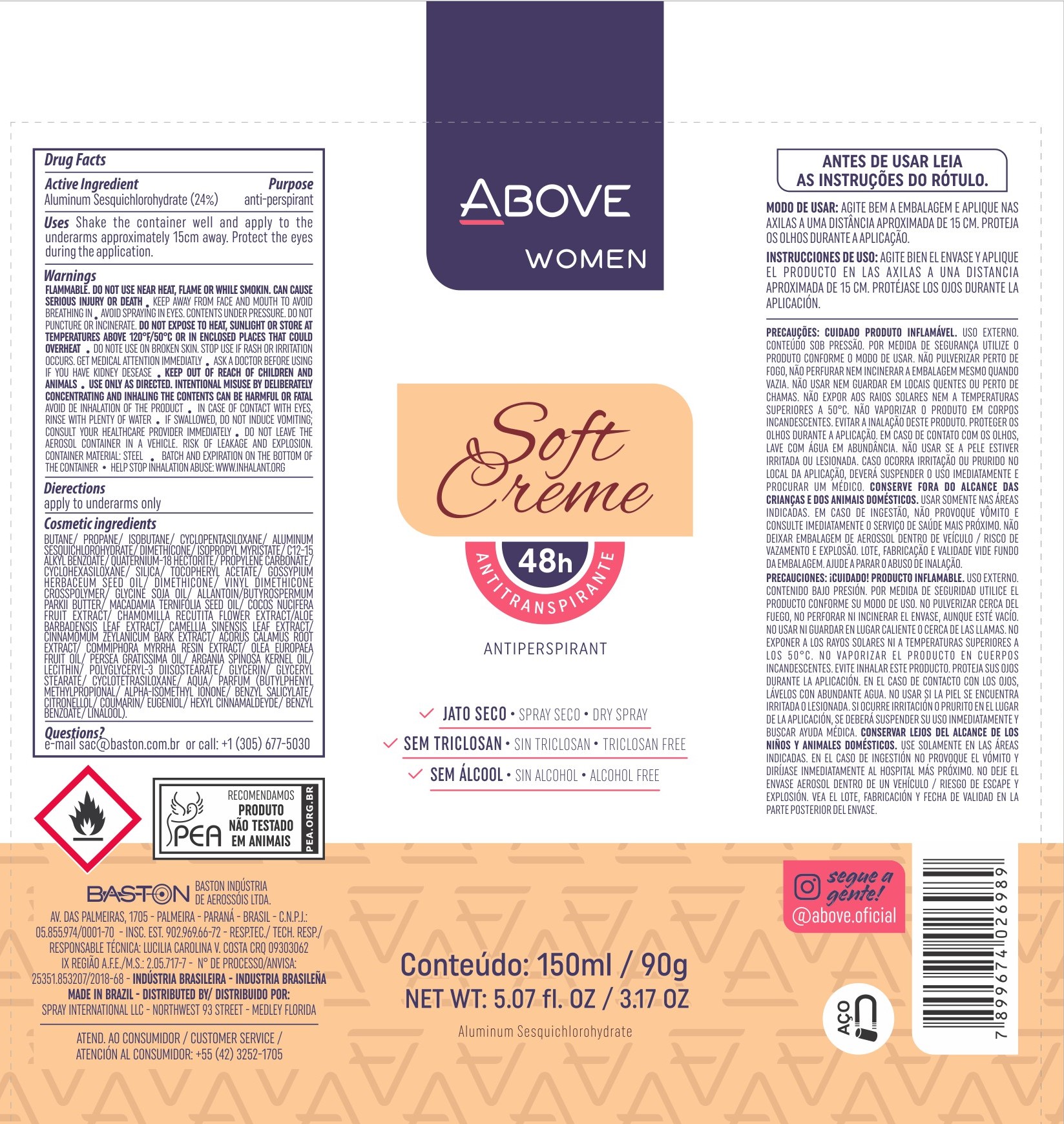 DRUG LABEL: Antiperspirant Above Soft Creme
NDC: 73306-1112 | Form: AEROSOL, SPRAY
Manufacturer: Baston Industria de Aerossóis Ltda
Category: otc | Type: HUMAN OTC DRUG LABEL
Date: 20241226

ACTIVE INGREDIENTS: ALUMINUM SESQUICHLOROHYDRATE 24 g/100 g
INACTIVE INGREDIENTS: .ALPHA.-TOCOPHEROL ACETATE; VINYL DIMETHICONE/METHICONE SILSESQUIOXANE CROSSPOLYMER; DISTEARDIMONIUM HECTORITE; GLYCERYL MONOSTEARATE; WATER; ISOPROPYL MYRISTATE; AVOCADO OIL; GREEN TEA LEAF; CINNAMON BARK OIL; CYCLOMETHICONE 5; SHEA BUTTER; PROPYLENE CARBONATE; MYRRH OIL; PROPANE; LECITHIN, SOYBEAN; ARGAN OIL; SILICA DIMETHYL SILYLATE; ALOE VERA LEAF; DIMETHICONE; GLYCERIN; LEVANT COTTON SEED; POLYGLYCERYL-3 DIISOSTEARATE; COCONUT; ACORUS CALAMUS ROOT; ALLANTOIN; BUTANE; CHAMOMILE; ISOBUTANE; MACADAMIA OIL

Antiperspirant Above Soft Creme Aerosol